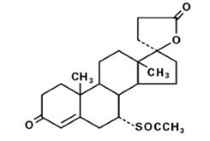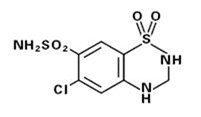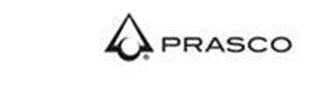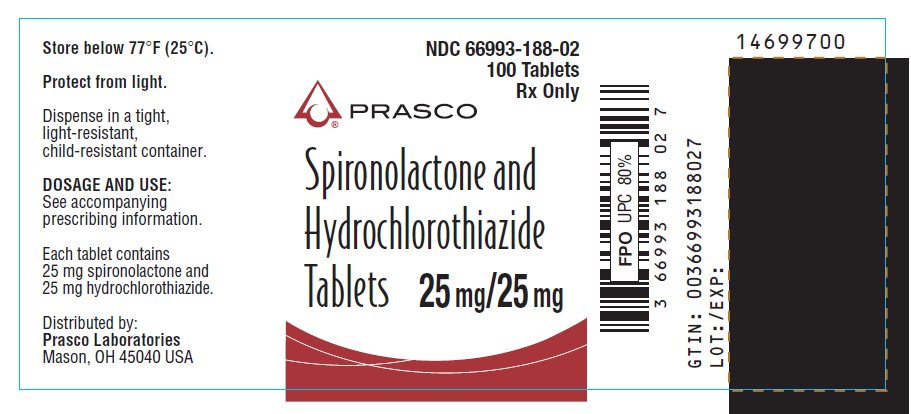 DRUG LABEL: Spironolactone and Hydrochlorothiazide
NDC: 66993-188 | Form: TABLET, FILM COATED
Manufacturer: Prasco Laboratories
Category: prescription | Type: HUMAN PRESCRIPTION DRUG LABEL
Date: 20260210

ACTIVE INGREDIENTS: SPIRONOLACTONE 25 mg/1 1; HYDROCHLOROTHIAZIDE 25 mg/1 1
INACTIVE INGREDIENTS: CALCIUM SULFATE, UNSPECIFIED FORM; STARCH, CORN; HYDROXYPROPYL CELLULOSE, UNSPECIFIED; HYPROMELLOSE, UNSPECIFIED; FERRIC OXIDE RED; MAGNESIUM STEARATE; POLYETHYLENE GLYCOL, UNSPECIFIED; POVIDONE, UNSPECIFIED; TITANIUM DIOXIDE

Spironolactone and
Hydrochlorothiazide
Tablets

DESCRIPTION

Spironolactone and hydrochlorothiazide oral tablets contain:

spironolactone | 25 mg
hydrochlorothiazide | 25 mg

Spironolactone, an aldosterone antagonist, is 17-hydroxy-7α-mercapto-3-oxo-17α-pregn-4-ene-21-carboxylic acid γ-lactone acetate and has the following structural formula:

Spironolactone is practically insoluble in water, soluble in alcohol, and freely soluble in benzene and in chloroform.

Hydrochlorothiazide, a diuretic and antihypertensive, is 6-chloro-3,4-dihydro-2H-1,2,4-benzothiadiazine-7-sulfonamide 1,1-dioxide and has the following structural formula:

Hydrochlorothiazide is slightly soluble in water and freely soluble in sodium hydroxide solution.

Inactive ingredients include calcium sulfate, corn starch, flavor, hydroxypropyl cellulose, hypromellose, iron oxide, magnesium stearate, polyethylene glycol, povidone, and titanium dioxide.

ACTIONS / CLINICAL PHARMACOLOGY

Mechanism of action

Spironolactone and hydrochlorothiazide tablets are a combination of two diuretic agents with different but complementary mechanisms and sites of action, thereby providing additive diuretic and antihypertensive effects. Additionally, the spironolactone component helps to minimize the potassium loss characteristically induced by the thiazide component.

The diuretic effect of spironolactone is mediated through its action as a specific pharmacologic antagonist of aldosterone, primarily by competitive binding of receptors at the aldosterone-dependent sodium-potassium exchange site in the distal convoluted renal tubule. Hydrochlorothiazide promotes the excretion of sodium and water primarily by inhibiting their reabsorption in the cortical diluting segment of the distal renal tubule.

Spironolactone and hydrochlorothiazide is effective in significantly lowering the systolic and diastolic blood pressure in many patients with essential hypertension, even when aldosterone secretion is within normal limits.

Both spironolactone and hydrochlorothiazide reduce exchangeable sodium, plasma volume, body weight, and blood pressure. The diuretic and antihypertensive effects of the individual components are potentiated when spironolactone and hydrochlorothiazide are given concurrently.

Pharmacokinetics

Spironolactone is rapidly and extensively metabolized. Sulfur-containing products are the predominant metabolites and are thought to be primarily responsible, together with spironolactone, for the therapeutic effects of the drug. The following pharmacokinetic data were obtained from 12 healthy volunteers following the administration of 100 mg of spironolactone (Aldactone® film-coated tablets [Aldactone is a trademark of Pfizer, Inc. and/or its affiliates.]) daily for 15 days. On the 15th day, spironolactone was given immediately after a low fat breakfast and blood was drawn thereafter.

 | Accumulation Factor:
 | AUC (0–24 hr, day 15)/AUC (0–24 hr, day 1) | Mean Peak Serum Concentration | Mean (SD) Post-Steady State Half-Life
7-α-(thiomethyl) spirolactone (TMS) | 1.25 | 391 ng/mL at 3.2 hr | 13.8 hr (6.4) (terminal)
6-β-hydroxy-7-α-(thiomethyl) spirolactone (HTMS) | 1.50 | 125 ng/mL at 5.1 hr | 15.0 hr (4.0) (terminal)
Canrenone (C) | 1.41 | 181 ng/mL at 4.3 hr | 16.5 hr (6.3) (terminal)
Spironolactone | 1.30 | 80 ng/mL at 2.6 hr | Approximately 1.4 hr (0.5) (β half-life)

The pharmacological activity of spironolactone metabolites in man is not known. However, in the adrenalectomized rat the antimineralocorticoid activities of the metabolites C, TMS, and HTMS, relative to spironolactone, were 1.10, 1.28, and 0.32, respectively. Relative to spironolactone, their binding affinities to the aldosterone receptors in rat kidney slices were 0.19, 0.86, and 0.06, respectively.

In humans, the potencies of TMS and 7-α-thiospirolactone in reversing the effects of the synthetic mineralocorticoid, fludrocortisone, on urinary electrolyte composition were 0.33 and 0.26, respectively, relative to spironolactone. However, since the serum concentrations of these steroids were not determined, their incomplete absorption and/or first-pass metabolism could not be ruled out as a reason for their reduced in vivo activities.

Spironolactone and its metabolites are more than 90% bound to plasma proteins. The metabolites are excreted primarily in the urine and secondarily in bile.

The effect of food on spironolactone absorption (two 100 mg Aldactone tablets) was assessed in a single dose study of 9 healthy, drug-free volunteers. Food increased the bioavailability of unmetabolized spironolactone by almost 100%. The clinical importance of this finding is not known.

Hydrochlorothiazide is rapidly absorbed following oral administration. Onset of action of hydrochlorothiazide is observed within one hour and persists for 6 to 12 hours. Hydrochlorothiazide plasma concentrations attain peak levels at one to two hours and decline with a half-life of four to five hours. Hydrochlorothiazide undergoes only slight metabolic alteration and is excreted in urine. It is distributed throughout the extracellular space, with essentially no tissue accumulation except in the kidney.

INDICATIONS AND USAGE

Spironolactone, an ingredient of spironolactone and hydrochlorothiazide tablets, has been shown to be a tumorigen in chronic toxicity studies in rats (see Precautions section). Spironolactone and hydrochlorothiazide tablets should be used only in those conditions described below. Unnecessary use of this drug should be avoided.

Spironolactone and hydrochlorothiazide tablets are indicated for:

Edematous conditions for patients with:

Congestive heart failure:

- For the management of edema and sodium retention when the patient is only partially responsive to, or is intolerant of, other therapeutic measures;
- The treatment of diuretic-induced hypokalemia in patients with congestive heart failure when other measures are considered inappropriate;
- The treatment of patients with congestive heart failure taking digitalis when other therapies are considered inadequate or inappropriate.

Cirrhosis of the liver accompanied by edema and/or ascites:

- Aldosterone levels may be exceptionally high in this condition. Spironolactone and hydrochlorothiazide tablets are indicated for maintenance therapy together with bed rest and the restriction of fluid and sodium.

The nephrotic syndrome:

- For nephrotic patients when treatment of the underlying disease, restriction of fluid and sodium intake, and the use of other diuretics do not provide an adequate response.

Essential hypertension:

- For patients with essential hypertension in whom other measures are considered inadequate or inappropriate;
- In hypertensive patients for the treatment of a diuretic-induced hypokalemia when other measures are considered inappropriate;
- Spironolactone and hydrochlorothiazide tablets are indicated for the treatment of hypertension, to lower blood pressure. Lowering blood pressure reduces the risk of fatal and nonfatal cardiovascular events, primarily strokes and myocardial infarctions. These benefits have been seen in controlled trials of antihypertensive drugs from a wide variety of pharmacologic classes, including the classes to which this drug principally belongs. There are no controlled trials demonstrating risk reduction with spironolactone and hydrochlorothiazide tablets.

Control of high blood pressure should be part of comprehensive cardiovascular risk management, including, as appropriate, lipid control, diabetes management, antithrombotic therapy, smoking cessation, exercise, and limited sodium intake. Many patients will require more than one drug to achieve blood pressure goals. For specific advice on goals and management, see published guidelines, such as those of the National High Blood Pressure Education Program's Joint National Committee on Prevention, Detection, Evaluation, and Treatment of High Blood Pressure (JNC).

Numerous antihypertensive drugs, from a variety of pharmacologic classes and with different mechanisms of action, have been shown in randomized controlled trials to reduce cardiovascular morbidity and mortality, and it can be concluded that it is blood pressure reduction, and not some other pharmacologic property of the drugs, that is largely responsible for those benefits. The largest and most consistent cardiovascular outcome benefit has been a reduction in the risk of stroke, but reductions in myocardial infarction and cardiovascular mortality also have been seen regularly.

Elevated systolic or diastolic pressure causes increased cardiovascular risk, and the absolute risk increase per mmHg is greater at higher blood pressures, so that even modest reductions of severe hypertension can provide substantial benefit. Relative risk reduction from blood pressure reduction is similar across populations with varying absolute risk, so the absolute benefit is greater in patients who are at higher risk independent of their hypertension (for example, patients with diabetes or hyperlipidemia), and such patients would be expected to benefit from more aggressive treatment to a lower blood pressure goal.

Some antihypertensive drugs have smaller blood pressure effects (as monotherapy) in black patients, and many antihypertensive drugs have additional approved indications and effects (e.g., on angina, heart failure, or diabetic kidney disease). These considerations may guide selection of therapy.

Usage in Pregnancy

The routine use of diuretics in an otherwise healthy woman is inappropriate and exposes mother and fetus to unnecessary hazard. Diuretics do not prevent development of toxemia of pregnancy, and there is no satisfactory evidence that they are useful in the treatment of developing toxemia.

Edema during pregnancy may arise from pathologic causes or from the physiologic and mechanical consequences of pregnancy. Spironolactone and hydrochlorothiazide tablets are indicated in pregnancy when edema is due to pathologic causes just as it is in the absence of pregnancy (however, see Precautions: Pregnancy). Dependent edema in pregnancy, resulting from restriction of venous return by the expanded uterus, is properly treated through elevation of the lower extremities and use of support hose; use of diuretics to lower intravascular volume in this case is unsupported and unnecessary. There is hypervolemia during normal pregnancy which is not harmful to either the fetus or the mother (in the absence of cardiovascular disease), but which is associated with edema, including generalized edema, in the majority of pregnant women. If this edema produces discomfort, increased recumbency will often provide relief. In rare instances, this edema may cause extreme discomfort that is not relieved by rest. In these cases, a short course of diuretics may provide relief and may be appropriate.

CONTRAINDICATIONS

Spironolactone and hydrochlorothiazide tablets are contraindicated in patients with anuria, acute renal insufficiency, significant impairment of renal excretory function, hypercalcemia, hyperkalemia, Addison's disease, and in patients who are allergic to thiazide diuretics or to other sulfonamide-derived drugs. Spironolactone and hydrochlorothiazide tablets may also be contraindicated in acute or severe hepatic failure.

WARNINGS

Potassium supplementation, either in the form of medication or as a diet rich in potassium, should not ordinarily be given in association with spironolactone and hydrochlorothiazide tablet therapy. Excessive potassium intake may cause hyperkalemia in patients receiving spironolactone and hydrochlorothiazide tablets (see Precautions: General).

Concomitant administration of spironolactone and hydrochlorothiazide tablets with the following drugs or potassium sources may lead to severe hyperkalemia:

- other potassium-sparing diuretics
- ACE inhibitors
- angiotensin II receptor antagonists
- aldosterone blockers
- non-steroidal anti-inflammatory drugs (NSAIDs), e.g., indomethacin
- heparin and low molecular weight heparin
- other drugs or conditions known to cause hyperkalemia
- potassium supplements
- diet rich in potassium
- salt substitutes containing potassium

Spironolactone and hydrochlorothiazide tablets should not be administered concurrently with other potassium-sparing diuretics. Spironolactone, when used with ACE inhibitors or indomethacin, even in the presence of a diuretic, has been associated with severe hyperkalemia. Extreme caution should be exercised when spironolactone and hydrochlorothiazide tablets are given concomitantly with these drugs (see Precautions: Drug interactions).

Spironolactone and hydrochlorothiazide tablets should be used with caution in patients with impaired hepatic function because minor alterations of fluid and electrolyte balance may precipitate hepatic coma.

Lithium generally should not be given with diuretics (see Precautions: Drug interactions).

Thiazides should be used with caution in severe renal disease. In patients with renal disease, thiazides may precipitate azotemia. Cumulative effects of the drug may develop in patients with impaired renal function.

Thiazides may add to or potentiate the action of other antihypertensive drugs.

Sensitivity reactions to thiazides may occur in patients with or without a history of allergy or bronchial asthma.

Sulfonamide derivatives, including thiazides, have been reported to exacerbate or activate systemic lupus erythematosus.

Acute Angle-Closure Glaucoma with or without Acute Myopia and Choroidal Effusions

Hydrochlorothiazide, a sulfonamide, can cause an idiosyncratic reaction, resulting in acute angle-closure glaucoma and elevated intraocular pressure with or without a noticeable acute myopic shift and/or choroidal effusions. Symptoms may include acute onset of decreased visual acuity or ocular pain and typically occur within hours to weeks of drug initiation. Untreated, the angle-closure glaucoma may result in permanent visual field loss. The primary treatment is to discontinue hydrochlorothiazide as rapidly as possible. Prompt medical or surgical treatments may need to be considered if the intraocular pressure remains uncontrolled. Risk factors for developing acute angle-closure glaucoma may include a history of sulfonamide or penicillin allergy.

PRECAUTIONS

General

Serum Electrolyte Abnormalities

Spironolactone can cause hyperkalemia. The risk of hyperkalemia may be increased in patients with renal insufficiency, diabetes mellitus or with concomitant use of drugs that raise serum potassium (see Drug Interactions). Hydrochlorothiazide can cause hypokalemia and hyponatremia. The risk of hypokalemia may be increased in patients with cirrhosis, brisk diuresis, or with concomitant use of drugs that lower serum potassium. Hypomagnesemia can result in hypokalemia which appears difficult to treat despite potassium repletion. Monitor serum electrolytes periodically.

Other Metabolic Disturbances

Hydrochlorothiazide may alter glucose tolerance and raise serum levels of cholesterol and triglycerides.

Hydrochlorothiazide may raise the serum uric acid level due to reduced clearance of uric acid and may cause or exacerbate hyperuricemia and precipitate gout in susceptible patients.

Hydrochlorothiazide decreases urinary calcium excretion and may cause elevations of serum calcium. Monitor calcium levels in patients with hypercalcemia receiving spironolactone and hydrochlorothiazide tablets.

Gynecomastia

Gynecomastia may develop in association with the use of spironolactone; physicians should be alert to its possible onset. The development of gynecomastia appears to be related to both dosage level and duration of therapy and is normally reversible when spironolactone and hydrochlorothiazide tablets are discontinued. In rare instances, some breast enlargement may persist when spironolactone and hydrochlorothiazide tablets are discontinued.

Somnolence

Somnolence and dizziness have been reported to occur in some patients. Caution is advised when driving or operating machinery until the response to initial treatment has been determined.

Information for patients

Patients who receive spironolactone and hydrochlorothiazide tablets should be advised to avoid potassium supplements and foods containing high levels of potassium including salt substitutes.

Non-melanoma Skin Cancer

Instruct patients taking hydrochlorothiazide to protect skin from the sun and undergo regular skin cancer screening.

Laboratory tests

Periodic determination of serum electrolytes to detect possible electrolyte imbalance should be done at appropriate intervals, particularly in the elderly and those with significant renal or hepatic impairments.

Drug interactions

ACE inhibitors, Angiotensin II receptor antagonists, aldosterone blockers, potassium supplements, heparin, low molecular weight heparin, and other drugs known to cause hyperkalemia:

Concomitant administration may lead to severe hyperkalemia.

Alcohol, barbiturates, or narcotics:

Potentiation of orthostatic hypotension may occur.

Antidiabetic drugs (e.g., oral agents, insulin):

Dosage adjustment of the antidiabetic drug may be required (see Precautions).

Corticosteroids, ACTH:

Intensified electrolyte depletion, particularly hypokalemia, may occur.

Pressor amines (e.g., norepinephrine):

Both spironolactone and hydrochlorothiazide reduce the vascular responsiveness to norepinephrine. Therefore, caution should be exercised in the management of patients subjected to regional or general anesthesia while they are being treated with spironolactone and hydrochlorothiazide tablets.

Skeletal muscle relaxants, nondepolarizing (e.g., tubocurarine):

Possible increased responsiveness to the muscle relaxant may result.

Lithium:

Lithium generally should not be given with diuretics. Diuretic agents reduce the renal clearance of lithium and add a high risk of lithium toxicity.

Nonsteroidal anti-inflammatory drugs (NSAIDs):

In some patients, the administration of an NSAID can reduce the diuretic, natriuretic, and antihypertensive effects of loop, potassium-sparing, and thiazide diuretics. Combination of NSAIDs, e.g., indomethacin, with potassium-sparing diuretics has been associated with severe hyperkalemia. Therefore, when spironolactone and hydrochlorothiazide tablets and NSAIDs are used concomitantly, the patient should be observed closely to determine if the desired effect of the diuretic is obtained.

Acetylsalicylic acid:

Acetylsalicylic acid may reduce the efficacy of spironolactone. Therefore, when spironolactone and hydrochlorothiazide and acetylsalicylic acid are used concomitantly, spironolactone and hydrochlorothiazide tablets may need to be titrated to higher maintenance dose and the patient should be observed closely to determine if the desired effect is obtained.

Digoxin:

Spironolactone has been shown to increase the half-life of digoxin. This may result in increased serum digoxin levels and subsequent digitalis toxicity. Monitor serum digoxin levels and adjust dose accordingly. Thiazide-induced electrolyte disturbances, i.e. hypokalemia, hypomagnesemia, increase the risk of digoxin toxicity, which may lead to fatal arrhythmic events (see Precautions).

Cholestyramine:

Hyperkalemic metabolic acidosis has been reported in patients given spironolactone concurrently with cholestyramine.

Abiraterone:

Spironolactone binds to the androgen receptor and may increase prostate‑specific antigen (PSA) levels in abiraterone-treated prostate cancer patients. Concomitant use of spironolactone is not recommended.

Mitotane:

Avoid concomitant use of spironolactone and hydrochlorothiazide tablets and mitotane. Spironolactone reduces mitotane plasma levels. The effect of concomitant spironolactone on the pharmacokinetics of mitotane has not been studied; however, patients exhibited significantly lower mitotane levels compared to those who did not receive concomitant spironolactone despite receiving higher mitotane doses.

Drug/Laboratory test interactions

Thiazides should be discontinued before carrying out tests for parathyroid function (see Precautions: General). Thiazides may also decrease serum PBI levels without evidence of alteration of thyroid function.

Several reports of possible interference with digoxin radioimmunoassays by spironolactone or its metabolites have appeared in the literature. Neither the extent nor the potential clinical significance of its interference (which may be assay specific) has been fully established.

Carcinogenesis, mutagenesis, impairment of fertility

Spironolactone

Orally administered spironolactone has been shown to be a tumorigen in dietary administration studies performed in Sprague Dawley rats, with its proliferative effects manifested on endocrine organs and the liver. In an 18-month study using doses of about 50, 150, and 500 mg/kg/day, there were statistically significant increases in benign adenomas of the thyroid and testes and, in male rats, a dose-related increase in proliferative changes in the liver (including hepatocytomegaly and hyperplastic nodules). In 24-month studies in which rats were administered doses of about 10, 30, 100, and 150 mg spironolactone/kg/day, the range of proliferative effects included significant increases in hepatocellular adenomas and testicular interstitial cell tumors in males, and significant increases in thyroid follicular cell adenomas and carcinomas in both sexes. There was also a statistically significant increase in benign uterine endometrial stromal polyps in females.

A dose-related (above 30 mg/kg/day) incidence of myelocytic leukemia was observed in rats fed daily doses of potassium canrenoate (a compound chemically similar to spironolactone and whose primary metabolite, canrenone, is also a major product of spironolactone in man) for a period of one year. In two year studies in the rat, oral administration of potassium canrenoate was associated with myelocytic leukemia and hepatic, thyroid, testicular, and mammary tumors.

Neither spironolactone nor potassium canrenoate produced mutagenic effects in tests using bacteria or yeast. In the absence of metabolic activation, neither spironolactone nor potassium canrenoate has been shown to be mutagenic in mammalian tests in vitro. In the presence of metabolic activation, spironolactone has been reported to be negative in some mammalian mutagenicity tests in vitro and inconclusive (but slightly positive) for mutagenicity in other mammalian tests in vitro. In the presence of metabolic activation, potassium canrenoate has been reported to test positive for mutagenicity in some mammalian tests in vitro, inconclusive in others, and negative in still others.

In a three-litter reproduction study in which female rats received dietary doses of 15 and 50 mg spironolactone/kg/day, there were no effects on mating and fertility, but there was a small increase in incidence of stillborn pups at 50 mg/kg/day. When injected into female rats (100 mg/kg/day for 7 days, i.p.), spironolactone was found to increase the length of the estrous cycle by prolonging diestrus during treatment and inducing constant diestrus during a two week posttreatment observation period. These effects were associated with retarded ovarian follicle development and a reduction in circulating estrogen levels, which would be expected to impair mating, fertility, and fecundity. Spironolactone (100 mg/kg/day), administered i.p. to female mice during a two week cohabitation period with untreated males, decreased the number of mated mice that conceived (effect shown to be caused by an inhibition of ovulation) and decreased the number of implanted embryos in those that became pregnant (effect shown to be caused by an inhibition of implantation), and at 200 mg/kg, also increased the latency period to mating.

Hydrochlorothiazide

Two year feeding studies in mice and rats conducted under the auspices of the National Toxicology Program (NTP) uncovered no evidence of a carcinogenic potential of hydrochlorothiazide in female mice (at doses of up to approximately 600 mg/kg/day) or in male and female rats (at doses of up to approximately 100 mg/kg/day). The NTP, however, found equivocal evidence for hepatocarcinogenicity in male mice.

Hydrochlorothiazide was not genotoxic in in vitro assays using strains TA 98, TA 100, TA 1535, TA 1537, and TA 1538 of Salmonella typhimurium (Ames assay) and in the Chinese Hamster Ovary (CHO) test for chromosomal aberrations, or in in vivo assays using mouse germinal cell chromosomes, Chinese hamster bone marrow chromosomes, and the Drosophila sex-linked recessive lethal trait gene. Positive test results were obtained only in the in vitro CHO Sister Chromatid Exchange (clastogenicity) and in the Mouse Lymphoma Cell (mutagenicity) assays, using concentrations of hydrochlorothiazide from 43 to 1300 μg/mL, and in the Aspergillus nidulans non-disjunction assay at an unspecified concentration.

Hydrochlorothiazide had no adverse effects on the fertility of mice and rats of either sex in studies wherein these species were exposed, via their diet, to doses of up to 100 and 4 mg/kg, respectively, prior to mating and throughout gestation.

Pregnancy

Teratogenic effects

Hydrochlorothiazide

Studies in which hydrochlorothiazide was orally administered to pregnant mice and rats during their respective periods of major organogenesis at doses up to 3000 and 1000 mg hydrochlorothiazide/kg, respectively, provided no evidence of harm to the fetus. There are, however, no adequate and well-controlled studies in pregnant women.

Spironolactone

Teratology studies with spironolactone have been carried out in mice and rabbits at doses of up to 20 mg/kg/day. On a body surface area basis, this dose in the mouse is substantially below the maximum recommended human dose and, in the rabbit, approximates the maximum recommended human dose. No teratogenic or other embryo-toxic effects were observed in mice, but the 20 mg/kg dose caused an increased rate of resorption and a lower number of live fetuses in rabbits. Because of its antiandrogenic activity and the requirement of testosterone for male morphogenesis, spironolactone may have the potential for adversely affecting sex differentiation of the male during embryogenesis. When administered to rats at 200 mg/kg/day between gestation days 13 and 21 (late embryogenesis and fetal development), feminization of male fetuses was observed. Offspring exposed during late pregnancy to 50 and 100 mg/kg/day doses of spironolactone exhibited changes in the reproductive tract including dose-dependent decreases in weights of the ventral prostate and seminal vesicle in males, ovaries and uteri that were enlarged in females, and other indications of endocrine dysfunction, that persisted into adulthood. There are no adequate and well-controlled studies with spironolactone and hydrochlorothiazide tablets in pregnant women. Spironolactone has known endocrine effects in animals including progestational and antiandrogenic effects. The antiandrogenic effects can result in apparent estrogenic side effects in humans, such as gynecomastia. Therefore, the use of spironolactone and hydrochlorothiazide tablets in pregnant women requires that the anticipated benefit be weighed against the possible hazards to the fetus.

Non-teratogenic effects

Spironolactone or its metabolites may, and hydrochlorothiazide does, cross the placental barrier and appear in cord blood. Therefore, the use of spironolactone and hydrochlorothiazide tablets in pregnant women requires that the anticipated benefit be weighed against possible hazards to the fetus. The hazards include fetal or neonatal jaundice, thrombocytopenia, and possibly other adverse reactions that have occurred in adults.

Nursing mothers

Canrenone, a major (and active) metabolite of spironolactone, appears in human breast milk. Because spironolactone has been found to be tumorigenic in rats, a decision should be made whether to discontinue the drug, taking into account the importance of the drug to the mother. If use of the drug is deemed essential, an alternative method of infant feeding should be instituted.

Thiazides are excreted in human milk in small amounts. Thiazides when given at high doses can cause intense diuresis which can in turn inhibit milk production. The use of spironolactone and hydrochlorothiazide tablets during breast feeding is not recommended. If spironolactone and hydrochlorothiazide tablets are used during breast feeding, doses should be kept as low as possible.

Pediatric use

Safety and effectiveness in pediatric patients have not been established.

ADVERSE REACTIONS

The following adverse reactions have been reported and, within each category (body system), are listed in order of decreasing severity.

Hydrochlorothiazide

Body as a whole: Weakness.

Cardiovascular: Hypotension including orthostatic hypotension (may be aggravated by alcohol, barbiturates, narcotics, or antihypertensive drugs).

Digestive: Pancreatitis, jaundice (intrahepatic cholestatic jaundice), diarrhea, vomiting, sialoadenitis, cramping, constipation, gastric irritation, nausea, anorexia.

Eye Disorders: Acute myopia and acute angle-closure glaucoma (see Warnings).

Hematologic: Aplastic anemia, agranulocytosis, leukopenia, hemolytic anemia, thrombocytopenia.

Hypersensitivity: Anaphylactic reactions, necrotizing angitis (vasculitis and cutaneous vasculitis), respiratory distress including pneumonitis and pulmonary edema, photosensitivity, fever, urticaria, rash, purpura.

Metabolic: Electrolyte imbalance (see Precautions), hyperglycemia, glycosuria, hyperuricemia.

Musculoskeletal: Muscle spasm.

Nervous system/psychiatric: Vertigo, paresthesias, dizziness, headache, restlessness.

Renal: Renal failure, renal dysfunction, interstitial nephritis (see Warnings).

Skin: Erythema multiforme, pruritus.

Special senses: Transient blurred vision, xanthopsia.

Spironolactone

Digestive: Gastric bleeding, ulceration, gastritis, diarrhea and cramping, nausea, vomiting.

Reproductive: Gynecomastia (see Precautions), inability to achieve or maintain erection, irregular menses or amenorrhea, postmenopausal bleeding, breast pain. Carcinoma of the breast has been reported in patients taking spironolactone but a cause and effect relationship has not been established.

Hematologic: Leukopenia (including agranulocytosis), thrombocytopenia.

Hypersensitivity: Fever, urticaria, maculopapular or erythematous cutaneous eruptions, anaphylactic reactions, vasculitis.

Metabolism: Hyperkalemia, electrolyte disturbances (see Warnings and Precautions).

Musculoskeletal: Leg cramps.

Nervous system/psychiatric: Lethargy, mental confusion, ataxia, dizziness, headache, drowsiness.

Liver/biliary: A very few cases of mixed cholestatic/hepatocellular toxicity, with one reported fatality, have been reported with spironolactone administration.

Renal: Renal dysfunction (including renal failure).

Skin: Stevens-Johnson Syndrome (SJS), toxic epidermal necrolysis (TEN), drug rash with eosinophilia and systemic symptoms (DRESS), alopecia, pruritus.

Post Marketing Experience

Non-melanoma Skin Cancer

Hydrochlorothiazide is associated with an increased risk of non-melanoma skin cancer. In a study conducted in the Sentinel System, increased risk was predominantly for squamous cell carcinoma (SCC) and in white patients taking large cumulative doses. The increased risk for SCC in the overall population was approximately 1 additional case per 16,000 patients per year, and for white patients taking a cumulative dose of ≥50,000 mg the risk increase was approximately 1 additional SCC case for every 6,700 patients per year.

OVERDOSAGE

The oral LD50 of spironolactone is greater than 1000 mg/kg in mice, rats, and rabbits. The oral LD50 of hydrochlorothiazide is greater than 10 g/kg in both mice and rats.

Acute overdosage of spironolactone may be manifested by drowsiness, mental confusion, maculopapular or erythematous rash, nausea, vomiting, dizziness, or diarrhea. Rarely, instances of hyponatremia, hyperkalemia (less commonly seen with spironolactone and hydrochlorothiazide tablets because the hydrochlorothiazide component tends to produce hypokalemia), or hepatic coma may occur in patients with severe liver disease, but these are unlikely due to acute overdosage.

However, because spironolactone and hydrochlorothiazide tablets contain both spironolactone and hydrochlorothiazide, the toxic effects may be intensified, and signs of thiazide overdosage may be present. These include electrolyte imbalance such as hypokalemia and/or hyponatremia. The potassium-sparing action of spironolactone may predominate and hyperkalemia may occur, especially in patients with impaired renal function. BUN determinations have been reported to rise transiently with hydrochlorothiazide. There may be CNS depression with lethargy or even coma.

Treatment

Induce vomiting or evacuate the stomach by lavage. There is no specific antidote. Treatment is supportive to maintain hydration, electrolyte balance, and vital functions.

Patients who have renal impairment may develop spironolactone-induced hyperkalemia. In such cases, spironolactone and hydrochlorothiazide tablets should be discontinued immediately. With severe hyperkalemia, the clinical situation dictates the procedures to be employed. These include the intravenous administration of calcium chloride solution, sodium bicarbonate solution, and/or the oral or parenteral administration of glucose with a rapid-acting insulin preparation. These are temporary measures to be repeated as required. Cationic exchange resins such as sodium polystyrene sulfonate may be orally or rectally administered. Persistent hyperkalemia may require dialysis.

DOSAGE AND ADMINISTRATION

Optimal dosage should be established by individual titration of the components.

Edema in adults (congestive heart failure, hepatic cirrhosis, or nephrotic syndrome)

The usual maintenance dose of spironolactone and hydrochlorothiazide tablets is 100 mg each of spironolactone and hydrochlorothiazide daily, administered in a single dose or in divided doses, but may range from 25 mg to 200 mg of each component daily depending on the response to the initial titration. In some instances it may be desirable to administer separate tablets of either spironolactone or hydrochlorothiazide in addition to spironolactone and hydrochlorothiazide tablets in order to provide optimal individual therapy.

The onset of diuresis with spironolactone and hydrochlorothiazide tablets occurs promptly and, due to prolonged effect of the spironolactone component, persists for two to three days after spironolactone and hydrochlorothiazide tablets are discontinued.

Essential hypertension

Although the dosage will vary depending on the results of titration of the individual ingredients, many patients will be found to have an optimal response to 50 mg to 100 mg each of spironolactone and hydrochlorothiazide daily, given in a single dose or in divided doses.

Concurrent potassium supplementation is not recommended when spironolactone and hydrochlorothiazide tablets are used in the long-term management of hypertension or in the treatment of most edematous conditions, since the spironolactone content of spironolactone and hydrochlorothiazide tablets is usually sufficient to minimize loss induced by the hydrochlorothiazide component.

HOW SUPPLIED

Spironolactone and hydrochlorothiazide tablets containing 25 mg of spironolactone and 25 mg of hydrochlorothiazide are round, tan, film coated, with G debossed on one side and 5014 on the other side, supplied as:

NDC Number | Size
66993-188-02 | bottle of 100

STORAGE AND HANDLING

Store below 77°F (25°C).

To report SUSPECTED ADVERSE REACTIONS, contact Prasco Laboratories at 1-866-525-0688 or FDA at 1-800-FDA-1088 or www.fda.gov/medwatch.

Distributed by:
Prasco Laboratories
Mason, OH 45040 USA

LAB-1466-4.0
Revised: November 2025

PRINCIPAL DISPLAY PANEL - 25 mg/25 mg Tablet Bottle Label

NDC 66993-188-02
100 Tablets
Rx Only

PRASCO

Spironolactone and
Hydrochlorothiazide
Tablets
25 mg/25 mg